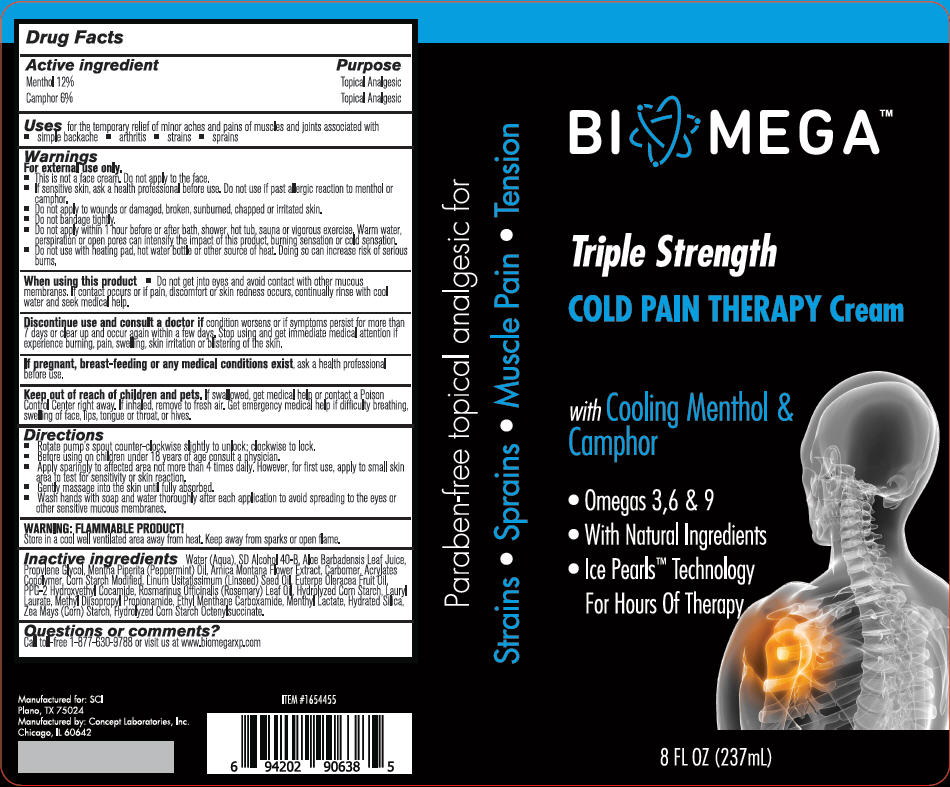 DRUG LABEL: BioMega 
NDC: 64058-344 | Form: CREAM
Manufacturer: Concept Laboratories, Inc.
Category: otc | Type: HUMAN OTC DRUG LABEL
Date: 20160203

ACTIVE INGREDIENTS: MENTHOL, UNSPECIFIED FORM 0.12 g/1 g; CAMPHOR (SYNTHETIC) 0.06 g/1 g
INACTIVE INGREDIENTS: WATER; ALOE VERA LEAF; PROPYLENE GLYCOL; PEPPERMINT OIL; ALCOHOL; STARCH, CORN; ARNICA MONTANA FLOWER; LINSEED OIL; ROSEMARY OIL; ACAI OIL; PPG-2 HYDROXYETHYL COCAMIDE; METHYL DIISOPROPYL PROPIONAMIDE; ETHYL MENTHANE CARBOXAMIDE; MENTHYL LACTATE, (-)-; LAURYL LAURATE

BioMega™
Cold Pain Therapy Cream

Drug Facts

ACTIVE INGREDIENT

Active ingredient | Purpose
Menthol 12% | Topical Analgesic
Camphor 6% | Topical Analgesic

Uses

for the temporary relief of minor aches and pains of muscles and joints associated with

- simple backache
- arthritis
- strains
- sprains

Warnings

For external use only.

DO NOT USE

- This is not a face cream. Do not apply to the face.
- If sensitive skin, ask a health professional before use. Do not use if past allergic reaction to menthol or camphor.
- Do not apply to wounds or damaged, broken, sunburned, chapped or irritated skin.
- Do not bandage tightly.
- Do not apply within 1 hour before or after bath, shower, hot tub, sauna or vigorous exercise. Warm water, perspiration or open pores can intensify the impact of this product, burning sensation or cold sensation.
- Do not use with heating pad, hot water bottle or other source of heat. Doing so can increase risk of serious burns.

When using this product

- Do not get into eyes and avoid contact with other mucous membranes. If contact occurs or if pain, discomfort or skin redness occurs, continually rinse with cool water and seek medical help.

ASK DOCTOR

Discontinue use and consult a doctor if condition worsens or if symptoms persist for more than 7 days or clear up and occur again within a few days. Stop using and get immediate medical attention if experience burning, pain, swelling, skin irritation or blistering of the skin.

PREGNANCY OR BREAST FEEDING

If pregnant, breast-feeding or any medical conditions exist, ask a health professional before use.

Keep out of reach of children and pets. If swallowed, get medical help or contact a Poison Control Center right away. If inhaled, remove to fresh air. Get emergency medical help if difficulty breathing, swelling of face, lips, tongue or throat, or hives.

Directions

- Rotate pump's spout counter-clockwise slightly to unlock; clockwise to lock.
- Before using on children under 18 years of age consult a physician.
- Apply sparingly to affected area not more than 4 times daily. However, for first use, apply to small skin area to test for sensitivity or skin reaction.
- Gently massage into the skin until fully absorbed.
- Wash hands with soap and water thoroughly after each application to avoid spreading to the eyes or other sensitive mucous membranes.

WARNING

FLAMMABLE PRODUCT!

Store in a cool well ventilated area away from heat. Keep away from sparks or open flame.

Inactive ingredients

Water (Aqua), SD Alcohol 40-B, Aloe Barbadensis Leaf Juice, Propylene Glycol, Mentha Piperita (Peppermint) Oil, Arnica Montana Flower Extract, Carbomer, Acrylates Copolymer, Corn Starch Modified, Linum Usitatissimum (Linseed) Seed Oil, Euterpe Oleracea Fruit Oil, PPG-2 Hydroxyethyl Cocamide, Rosmarinus Officinalis (Rosemary) Leaf Oil, Hydrolyzed Corn Starch, Lauryl Laurate, Methyl Diisopropyl Propionamide, Ethyl Menthane Carboxamide, Menthyl Lactate, Hydrated Silica, Zea Mays (Corn) Starch, Hydrolyzed Corn Starch Octenylsuccinate.

Questions or comments?

Call toll-free 1-877-630-9788 or visit us at www.biomegarxp.com

Manufactured by: Concept Laboratories, Inc. Chicago, IL 60642

PRINCIPAL DISPLAY PANEL - 237 mL Bottle Label

BIOMEGA™

Triple Strength

COLD PAIN THERAPY Cream

with Cooling Menthol &
Camphor

- Omegas 3,6 & 9
- With Natural Ingredients
- Ice Pearls™ Technology
  For Hours Of Therapy

8 FL OZ (237mL)